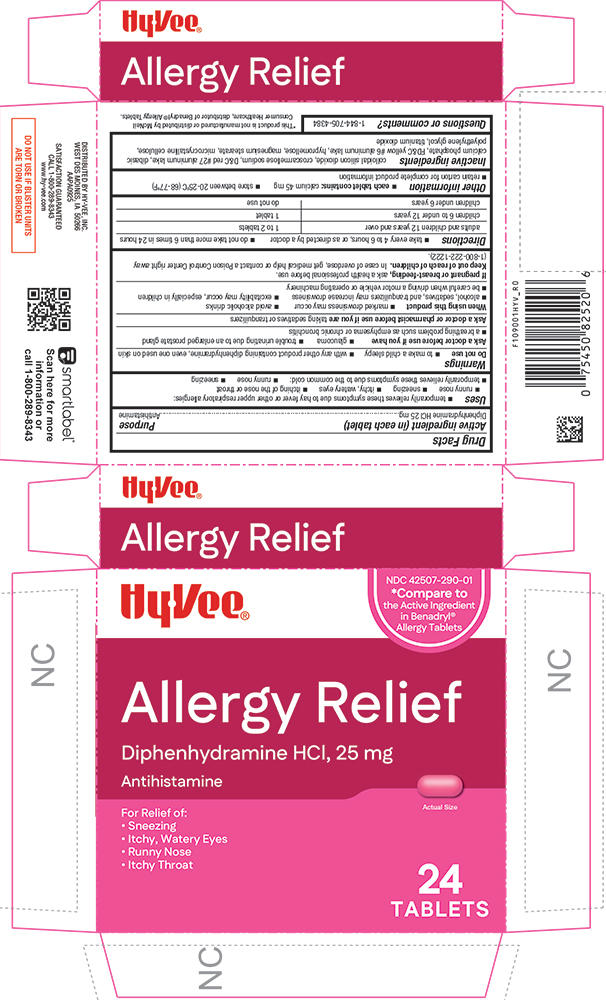 DRUG LABEL: Allergy Relief
NDC: 42507-290 | Form: TABLET, COATED
Manufacturer: HYVEE INC
Category: otc | Type: HUMAN OTC DRUG LABEL
Date: 20260113

ACTIVE INGREDIENTS: DIPHENHYDRAMINE HYDROCHLORIDE 25 mg/1 1
INACTIVE INGREDIENTS: SILICON DIOXIDE; CROSCARMELLOSE SODIUM; D&C RED NO. 27; CALCIUM PHOSPHATE, DIBASIC, ANHYDROUS; FD&C YELLOW NO. 6; HYPROMELLOSES; MAGNESIUM STEARATE; CELLULOSE, MICROCRYSTALLINE; POLYETHYLENE GLYCOL, UNSPECIFIED; TITANIUM DIOXIDE; ALUMINUM OXIDE

1090-HYV-2025-1022

Drug Facts

Active ingredient (in each tablet)

Diphenhydramine HCl 25 mg

Purpose

Antihistamine

Uses

- temporarily relieves these symptoms due to hay fever or other upper respiratory allergies:
  - runny nose
  - sneezing
  - itchy, watery eyes
  - itching of the nose or throat
- temporarily relieves these symptoms due to the common cold:
  - runny nose
  - sneezing

Warnings

Do not use

- to make a child sleepy
- with any other product containing diphenhydramine, even one used on skin

Ask a doctor before use if you have

- glaucoma
- a breathing problem such as emphysema or chronic bronchitis
- trouble urinating due to an enlarged prostate gland

Ask a doctor or pharmacist before use if you aretaking sedatives or tranquilizers

When using this product

- marked drowsiness may occur
- avoid alcoholic drinks
- alcohol, sedatives, and tranquilizers may increase drowsiness
- be careful when driving a motor vehicle or operating machinery
- excitability may occur, especially in children

PREGNANCY OR BREAST FEEDING

If pregnant or breast-feeding,ask a health professional before use.

Keep out of reach of children.In case of overdose, get medical help or contact a Poison Control Center right away (1-800-222-1222).

Directions

- take every 4 to 6 hours, or as directed by a doctor
- do not take more than 6 times in 24 hours

adults and children 12 years and over | 1 to 2 tablets
children 6 to under 12 years | 1 tablet
children under 6 years | do not use

Other information

- each tablet contains:calcium 45 mg
- store between 20-25°C (68-77°F)
- retain carton for complete product information

Inactive ingredients

colloidal silicon dioxide, croscarmellose sodium, D&C red #27 aluminum lake, dibasic calcium phosphate, FD&C yellow #6 aluminum lake, hypromellose, magnesium stearate, microcrystalline cellulose, polyethylene glycol, titanium dioxide

Questions or comments?

1-844-705-4384

PRINCIPAL DISPLAY PANEL

HyVee®

NDC 42507-290-01

*Compare to the Active Ingredient in Benadryl® Allergy Tablets

Allergy Relief

Diphenhydramine HCl, 25 mg

Antihistamine

For Relief of:

• Sneezing

• Itchy, Watery Eyes

• Runny Nose

• Itchy Throat

Actual Size

24 TABLETS